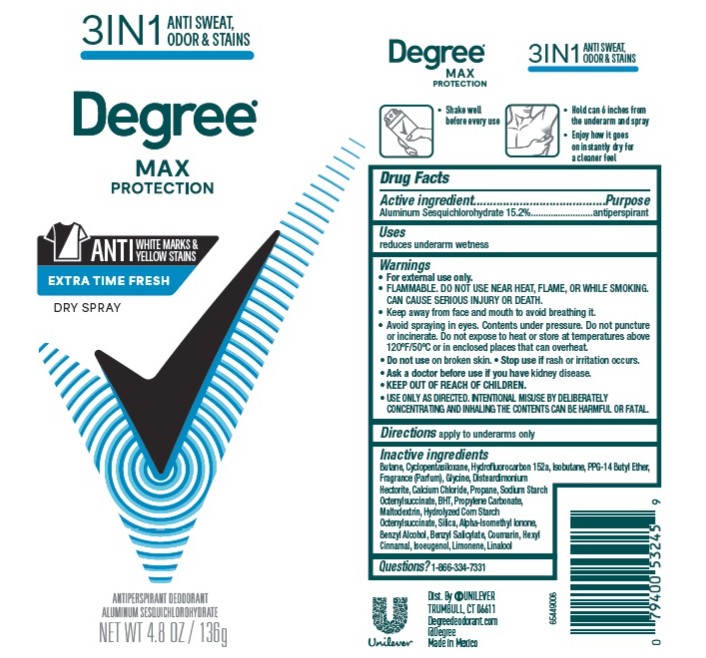 DRUG LABEL: Degree
NDC: 64942-2422 | Form: SPRAY
Manufacturer: Conopco d/b/a Unilever
Category: otc | Type: HUMAN OTC DRUG LABEL
Date: 20260116

ACTIVE INGREDIENTS: ALUMINUM SESQUICHLOROHYDRATE 15.2 g/100 g
INACTIVE INGREDIENTS: HEXYL CINNAMAL; LIMONENE, (+)-; BUTANE; MALTODEXTRIN; GLYCINE; PROPYLENE CARBONATE; ALPHA-ISOMETHYL IONONE; ISOEUGENOL; PROPANE; BHT; BENZYL ALCOHOL; COUMARIN; BENZYL SALICYLATE; SILICA; LINALOOL; CYCLOPENTASILOXANE; HYDROFLUOROCARBON 152A; DISTEARDIMONIUM HECTORITE; CALCIUM CHLORIDE; PPG-14 BUTYL ETHER; ISOBUTANE

Degree Max Protection Extra Time Fresh Dry Spray Antiperspirant Deodorant

DESCRIPTION

Degree Max Protection Extra Time Fresh Dry Spray Antiperspirant Deodorant

ACTIVE INGREDIENT

Aluminum Sesquichlorohydrate 15.2%

PURPOSE

Antiperspirant

INDICATIONS AND USAGE

reduces underarm wetness

WARNINGS

• For external use only.
• FLAMMABLE. DO NOT USE NEAR HEAT, FLAME, OR WHILE SMOKING. CAN CAUSE SERIOUS INJURY OR DEATH.
• Keep away from face and mouth to avoid breathing it.
• Avoid spraying in eyes. Contents under pressure. Do not puncture or incinerate. Do not expose to heat or store at temperatures above 120°F/50°C or in enclosed places that can overheat.
• Do not use on broken skin. • Stop use if rash or irritation occurs.• Ask a doctor before use if you have kidney disease. • USE ONLY AS DIRECTED. INTENTIONAL MISUSE BY DELIBERATELY CONCENTRATING AND INHALING THE CONTENTS CAN BE HARMFUL OR FATAL.
Help stop inhalation abuse. For information visit www.consumered.org

• KEEP OUT OF REACH OF CHILDREN.

DOSAGE AND ADMINISTRATION

apply to underarms only

INACTIVE INGREDIENT

Butane, Cyclopentasiloxane, Hydrofluorocarbon 152a, Isobutane, PPG-14 Butyl Ether, Fragrance (Parfum), Glycine, Disteardimonium
Hectorite, Calcium Chloride, Propane, Sodium Starch Octenylsuccinate, BHT, Propylene Carbonate, Maltodextrin, Hydrolyzed Corn Starch Octenylsuccinate, Silica, Alpha-Isomethyl Ionone, Benzyl Alcohol, Benzyl Salicylate, Coumarin, Hexyl Cinnamal, Isoeugenol, Limonene, Linalool

QUESTIONS

1-800-761-3683